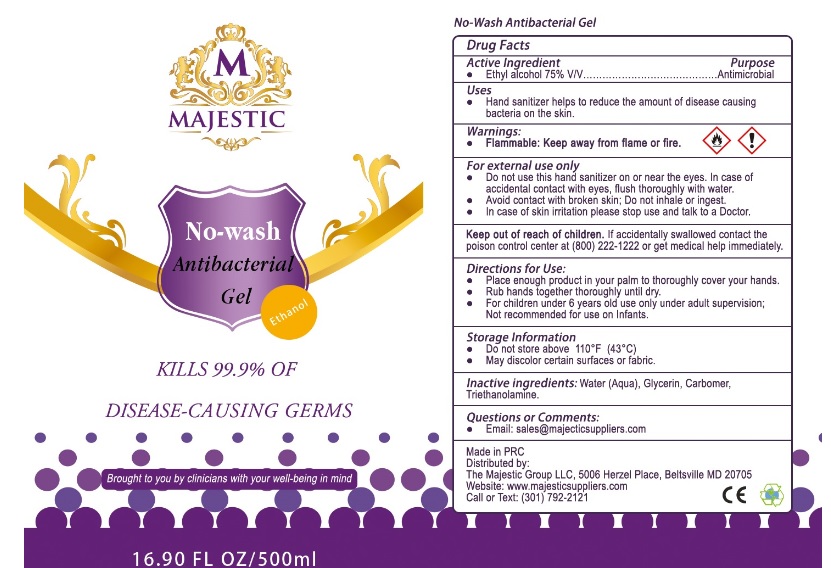 DRUG LABEL: NO-WASH ANTIBACTERIAL
NDC: 77331-001 | Form: GEL
Manufacturer: MAJESTIC GROUP LLC
Category: otc | Type: HUMAN OTC DRUG LABEL
Date: 20200511

ACTIVE INGREDIENTS: ALCOHOL 75 mL/100 mL
INACTIVE INGREDIENTS: WATER; GLYCERIN; CARBOMER HOMOPOLYMER, UNSPECIFIED TYPE; TROLAMINE

NO-WASH ANTIBACTERIAL GEL

Active Ingredient

Ethyl Alcohol

Purpose

Antimicrobial

Uses

Hand-Sanitizer helps to reduce the amount of disease causing bacteria on the skin

Warnings

Flammable. Keep away from fire or flame.

For external use only.

- Do not use this hand sanitizer on or near the eyes.In case of accidental contact, flush eyes thoroughtly with water.
- Do not use on broken skin: Do not inhale or ingest.
- In case of skin irritation please stop use and talk to doctor.

Directions

- Place enough product in your palm to thoroughly cover your hands.
- Rub hands togerher thoroughly until dry.
- For children under 6 years old use only under adult supevision :Not recommended for use on infants.

Keep out of reach of children

If accidentally swallowed, contact the Poison Control Center or get medical help immediately.

Other Information

- Do not store above 110°F (43°C)
- May discolor certain fabrics or surfaces

Inactive Ingredient

Water(Aqua),Carbomer,Glycerin,Triethanolamine